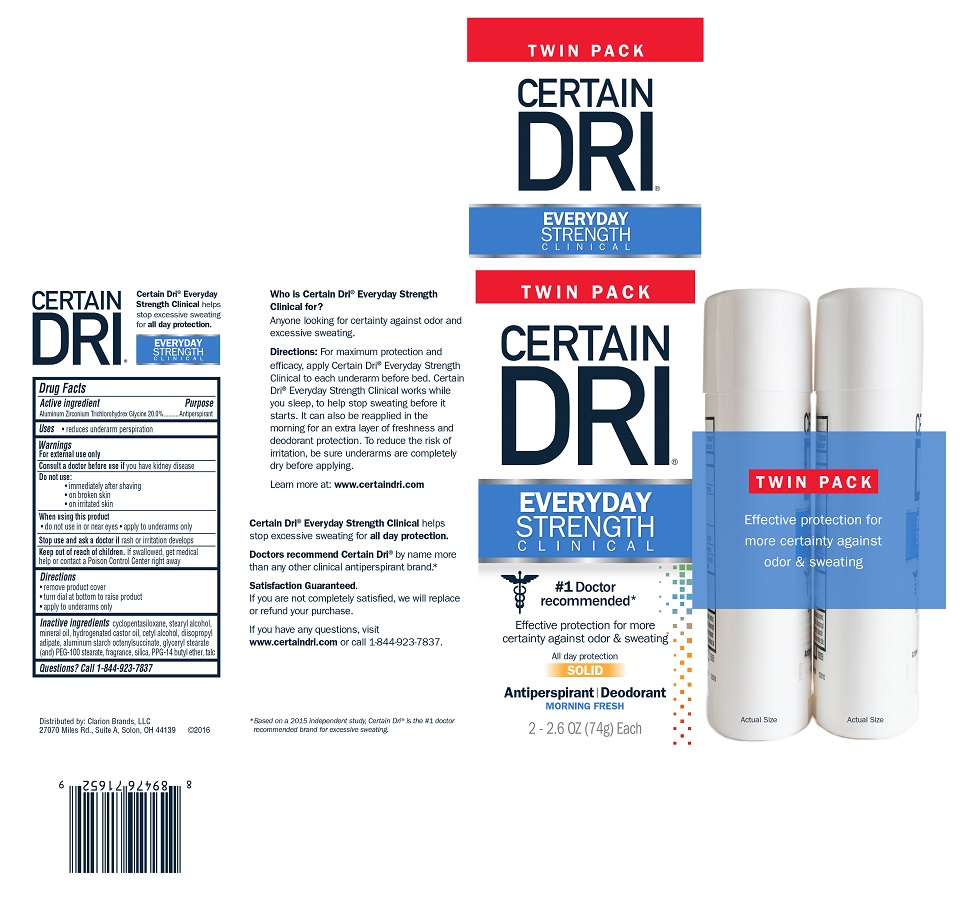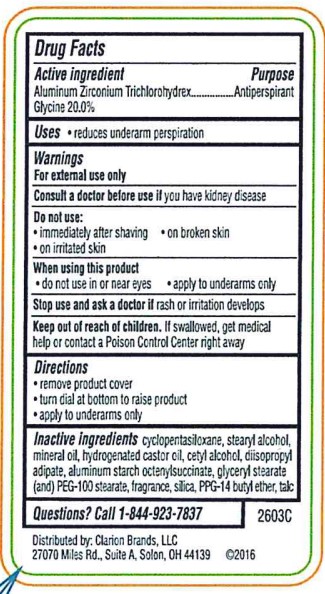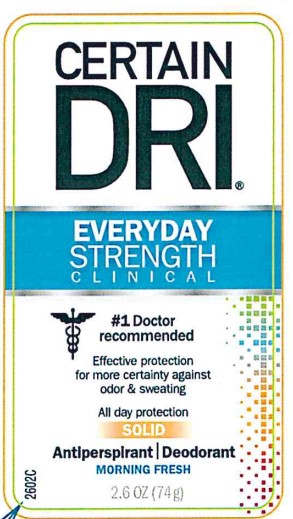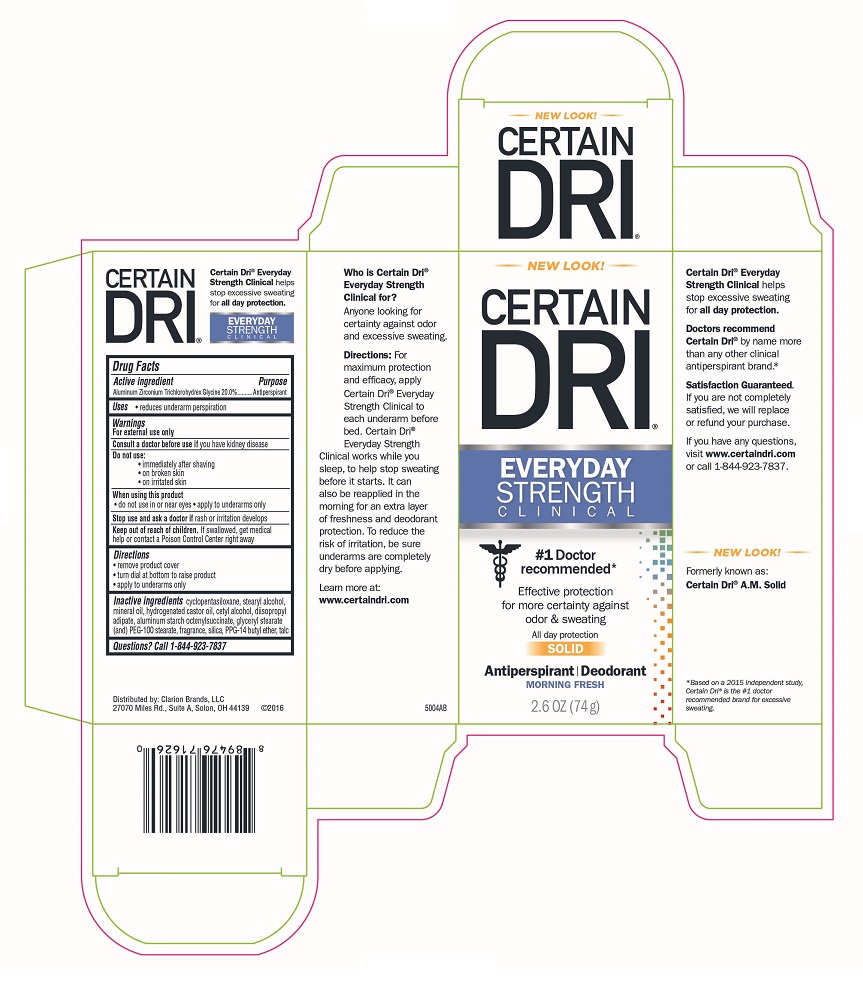 DRUG LABEL: Certain Dri Everyday Strength Clinical
NDC: 69693-719 | Form: STICK
Manufacturer: Clarion Brands, LLC
Category: otc | Type: HUMAN OTC DRUG LABEL
Date: 20251223

ACTIVE INGREDIENTS: ALUMINUM ZIRCONIUM TRICHLOROHYDREX GLY 20 g/100 g
INACTIVE INGREDIENTS: CYCLOMETHICONE 5; STEARYL ALCOHOL; MINERAL OIL; HYDROGENATED CASTOR OIL; CETYL ALCOHOL; DIISOPROPYL ADIPATE; ALUMINUM STARCH OCTENYLSUCCINATE; GLYCERYL MONOSTEARATE; PEG-100 STEARATE; SILICON DIOXIDE; PPG-14 BUTYL ETHER; TALC

Drug Facts

Active Ingredient | Purpose
Aluminum Zirconium Trichlorohydrex Glycine 20% | Antiperspirant

Uses

- reduces underarm perspiration

Warnings

For external use only

ASK DOCTOR

Consult a Doctor before useif you have kidney disease

Do not use:

- immediately after shaving
- on broken skin
- on irritated skin

When using this product

- do not use in or near eyes
- apply to underarms only

Stop use and ask a doctor ifrash or irritation develops

Keep out of reach of children.If swallowed, get medical help or contact a Poison Control Center right away

Directions

- remove product cover
- turn dial at bottom to raise product
- apply to underarms only

Inactive ingredients

cyclopentasiloxane, stearyl alcohol, mineral oil, hydrogenated castor oil, cetyl alcohol, diisopropyl adipate, aluminum starch octenylsuccinate, glyceryl stearate (and) PEG-100 stearate, fragrance, silica, PPG-14 butyl ether, talc

Questions? Call 1-844-923-7837

PRINCIPAL DISPLAY PANEL

CERTAIN
DRI®
EVERYDAY
STRENGTH
CLINICAL
#1 Doctor recommended
Effective protection
for more certainty against
odor & sweating
All day protection
SOLID
Antiperspirant | Deodorant
MORNING FRESH
2.6 OZ. (74 g)
2602C

Distributed by: Clarion Brands, LLC
27070 Miles Rd., Suite A, Solon, OH 44139 ©2016
2603C

TWIN PACK
CERTAIN
DRI®
EVERYDAY
STRENGTH
CLINICAL
#1 Doctor recommended*
Effective protection for more certainty against odor & sweating
All day protection
SOLID
Antiperspirant | Deodorant
MORNING FRESH
2 - 2.6 OZ. (74 g) Each
Who is Certain Dri®Everyday Strength Clinical for?
Anyone looking for certainty against odor and excessive sweating.
Directions:For maximum protection and efficacy, apply Certain Dri®Everyday Strength Clinical to each underarm before bed. Certain Dri®Everyday Strength Clinical works while you sleep, to help stop sweating before it starts. It can also be reapplied in the morning for an extra layer of freshness and deodorant protection. To reduce the risk of irritation, be sure underarms are completely dry before applying.
Learn more at: www.certaindri.com
Certain Dri®Everyday Strength Clinical helps stop excessive sweating for all day protection.
Doctors recommend Certain Dri® by name more than any other clinical antiperspirant brand.*
Satisfaction Guaranteed.
If you are not completely satisfied, we will replace or refund your purchase.
If you have any questions, visit www.certaindri.comor call 1-844-923-7837.
*Based on a 2015 independent study, Certain Dri®is the #1 doctor recommended brand for excessive sweating.
Certain Dri®Everyday Strength Clinical helps stop excessive sweating for all day protection.
TWIN PACK
Effective protection for more certainty against odor & sweating
Distributed by: Clarion Brands, LLC
27070 Miles Rd., Suite A, Solon, OH 44139 ©2016

NEW LOOK!
CERTAIN
DRI®
EVERYDAY
STRENGTH
CLINICAL
#1 Doctor recommended*
Effective protection for more certainty against odor & sweating
All day protection
SOLID
Antiperspirant | Deodorant
MORNING FRESH
2.6 OZ. (74 g)
Who is Certain Dri®Everyday Strength Clinical for?
Anyone looking for certainty against odor and excessive sweating.
Directions:For maximum protection and efficacy, apply Certain Dri®Everyday Strength Clinical to each underarm before bed. Certain Dri®Everyday Strength Clinical works while you sleep, to help stop sweating before it starts. It can also be reapplied in the morning for an extra layer of freshness and deodorant protection. To reduce the risk of irritation, be sure underarms are completely dry before applying.
Learn more at:
www.certaindri.com
5004AB
Certain Dri®Everyday Strength Clinical helps stop excessive sweating for all day protection.
Doctors recommend Certain Dri® by name more than any other clinical antiperspirant brand.*
Satisfaction Guaranteed.
If you are not completely satisfied, we will replace or refund your purchase.
If you have any questions, visit www.certaindri.comor call 1-844-923-7837.
NEW LOOK!
Formerly known as: Certain Dri®A.M. Solid
*Based on a 2015 independent study, Certain Dri®is the #1 doctor recommended brand for excessive sweating.
Certain Dri®Everyday Strength Clinical helps stop excessive sweating for all day protection.
Distributed by: Clarion Brands, LLC
27070 Miles Rd., Suite A, Solon, OH 44139 ©2016